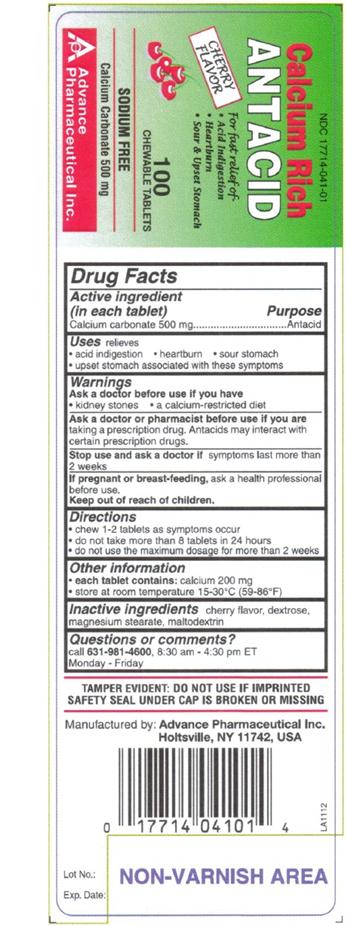 DRUG LABEL: ANTACID
NDC: 17714-041 | Form: TABLET, CHEWABLE
Manufacturer: Advance Pharmaceutical Inc.
Category: otc | Type: HUMAN OTC DRUG LABEL
Date: 20241226

ACTIVE INGREDIENTS: CALCIUM CARBONATE 500 mg/1 1
INACTIVE INGREDIENTS: DEXTROSE; MAGNESIUM STEARATE; MALTODEXTRIN; CHERRY

Calcium Rich

Active Ingredient

(in each tablet)

Calcium Carbonate 500 mg

Purpose

Antacid

Uses

relieves

- acid indigestion
- heartburn
- sour stomach
- upset stomach associated with these symptoms

Warnings

Ask a doctor before use if you have

- kidney stones
- a calcium-restricted diet
  ask a doctor or pharmacist before use if you aretaking a prescription drug. Antacids may interact with certain prescription drugs.
  Stop use and ask a doctorif symptoms last more than 2 weeks.
  If pregnant or breast-feeding,ask a health professional before use.

Keep out of reach of children.

In case of overdose, get medical help or contact a Poison Control Center right away.

Directions

- chew 1-2 tablets as symptoms occurs.
- do not take more than 8 tablets in 24 hours
- do not use the maximum dosage for more than 2 weeks

Other Information

- each tablet contains:calcium 200 mg
- store at room temperature 15-30 °C (59-86 °F)

Inactive Ingredients

Cherry flavor, dextrose, magnesium stearate, maltodextrin

Questions or Comments

Call 631-981-4600, Monday-Friday, 8.30 am – 4.30 pm ET

TAMPER EVIDENT: DO NOT USE IF IMPRINTED SAFETY SEAL UNDER CAP IS BROKEN OR MISSING

Manufactured by: Advance Pharmaceutical Inc. Holtsville, NY 11742

PACKAGE LABEL.PRINCIPAL DISPLAY PANEL

Calcium Carbonate 500 mg

Antacid tablets

NDC: 17714-041-01 – 100 COUNT